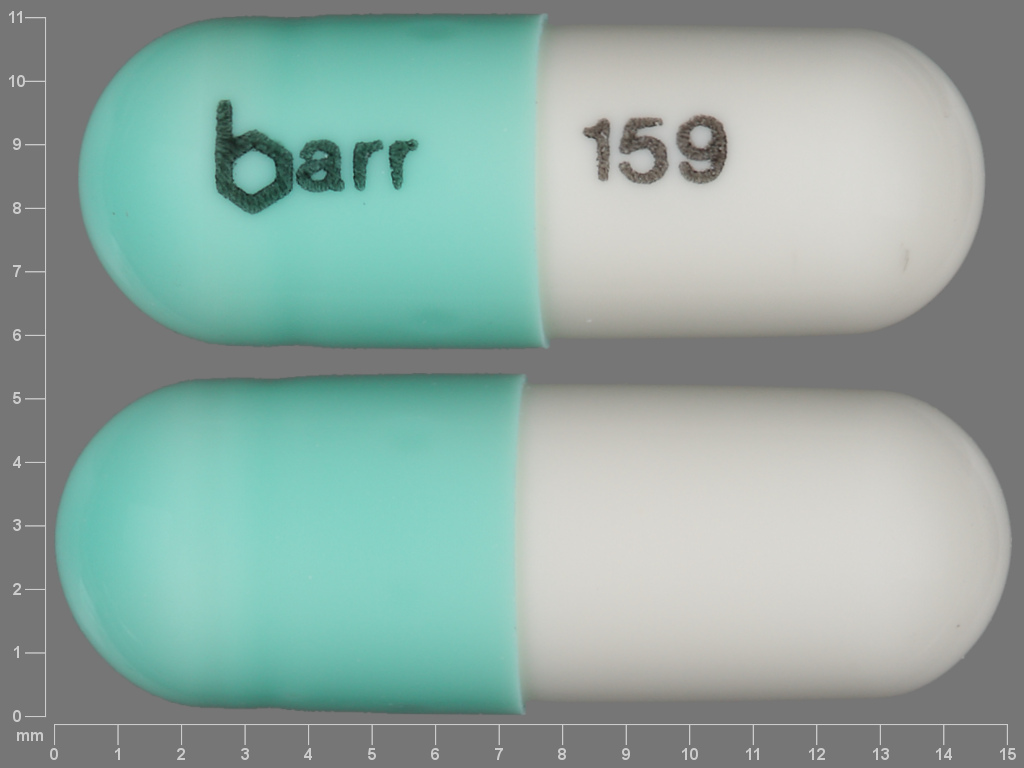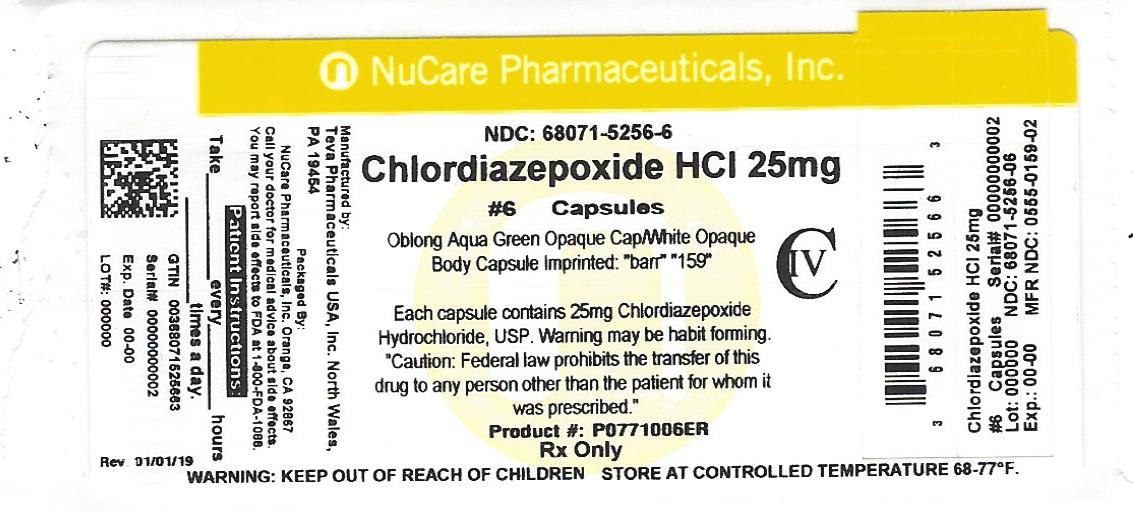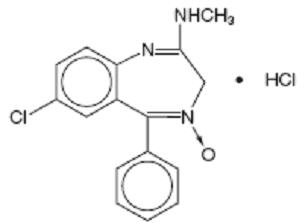 DRUG LABEL: Chlordiazepoxide Hydrochloride
NDC: 68071-5256 | Form: CAPSULE
Manufacturer: NuCare Pharmaceuticals,Inc.
Category: prescription | Type: HUMAN PRESCRIPTION DRUG LABEL
Date: 20240717
DEA Schedule: CIV

ACTIVE INGREDIENTS: CHLORDIAZEPOXIDE HYDROCHLORIDE 25 mg/1 1
INACTIVE INGREDIENTS: ANHYDROUS LACTOSE; D&C YELLOW NO. 10; FD&C BLUE NO. 1; GELATIN, UNSPECIFIED; HYDROGENATED COTTONSEED OIL; MICROCRYSTALLINE CELLULOSE; SHELLAC; TITANIUM DIOXIDE; FD&C BLUE NO. 2; INDIGOTINDISULFONATE SODIUM; FD&C RED NO. 40; PROPYLENE GLYCOL; FERROSOFERRIC OXIDE

Chlordiazepoxide Hydrochloride Capsules USP CIV
Rx only

WARNING: RISKS FROM CONCOMITANT USE WITH OPIOIDS; ABUSE, MISUSE, AND ADDICTION; and DEPENDENCE AND WITHDRAWAL REACTIONS

ul>

- Concomitant use of benzodiazepines and opioids may result in profound sedation, respiratory depression, coma, and death. Reserve concomitant prescribing of these drugs for patients for whom alternative treatment options are inadequate. Limit dosages and durations to the minimum required. Follow patients for signs and symptoms of respiratory depression and sedation (see WARNINGS and PRECAUTIONS).
- The use of benzodiazepines, including chlordiazepoxide hydrochloride capsules, exposes users to risks of abuse, misuse, and addiction, which can lead to overdose or death. Abuse and misuse of benzodiazepines commonly involve concomitant use of other medications, alcohol, and/or illicit substances, which is associated with an increased frequency of serious adverse outcomes. Before prescribing chlordiazepoxide hydrochloride capsules and throughout treatment, assess each patient’s risk for abuse, misuse, and addiction (see WARNINGS).
- The continued use of benzodiazepines, including chlordiazepoxide hydrochloride capsules, may lead to clinically significant physical dependence. The risks of dependence and withdrawal increase with longer treatment duration and higher daily dose. Abrupt discontinuation or rapid dosage reduction of chlordiazepoxide hydrochloride capsules after continued use may precipitate acute withdrawal reactions, which can be life-threatening. To reduce the risk of withdrawal reactions, use a gradual taper to discontinue chlordiazepoxide hydrochloride capsules or reduce the dosage (see DOSAGE AND ADMINISTRATION and WARNINGS).

DESCRIPTION

Chlordiazepoxide hydrochloride is the prototype for the benzodiazepine compounds. It is a versatile therapeutic agent of proven value for the relief of anxiety. Chlordiazepoxide hydrochloride is among the safer of the effective psychopharmacologic compounds available, as demonstrated by extensive clinical evidence.

Chlordiazepoxide hydrochloride is 7-chloro-2- (methylamino)-5-phenyl-3 H-1,4-benzodiazepine 4-oxide hydrochloride. A white to practically white crystalline substance, it is soluble in water. It is unstable in solution and the powder must be protected from light. The structural formula is:

C16H14ClN3O • HCl M.W. 336.22

Each capsule, for oral administration, contains either 5 mg, 10 mg or 25 mg of chlordiazepoxide hydrochloride, USP and has the following inactive ingredients: anhydrous lactose, D&C yellow no. 10, FD&C blue no. 1, FD&C blue no. 1 aluminum lake, gelatin, hydrogenated vegetable oil, microcrystalline cellulose, pharmaceutical glaze, and titanium dioxide. The 5 mg and 25 mg also contain D&C yellow no. 10 aluminum lake, FD&C blue no. 2 aluminum lake, FD&C red no. 40 aluminum lake, propylene glycol, and synthetic black iron oxide. In addition, the 5 mg contains D&C red no. 33 and the 10 mg also contains butyl paraben, edetate calcium disodium, dimethyl polysiloxane, ethylene glycol monoethyl ether, FD&C red no. 40, methyl paraben, propyl paraben, sodium, sodium lauryl sulfate, sodium propionate, and soya lecithin.

CLINICAL PHARMACOLOGY

Chlordiazepoxide HCl has antianxiety, sedative, appetite-stimulating and weak analgesic actions. The precise mechanism of action is not known. The drug blocks EEG arousal from stimulation of the brain stem reticular formation. It takes several hours for peak blood levels to be reached and the half-life of the drug is between 24 and 48 hours. After the drug is discontinued plasma levels decline slowly over a period of several days. Chlordiazepoxide is excreted in the urine, with 1% to 2% unchanged and 3% to 6% as conjugate.

Animal Pharmacology

The drug has been studied extensively in many species of animals and these studies are suggestive of action on the limbic system of the brain, which recent evidence indicates is involved in emotional responses.

Hostile monkeys were made tame by oral drug doses which did not cause sedation. Chlordiazepoxide HCl revealed a “taming” action with the elimination of fear and aggression. The taming effect of chlordiazepoxide HCl was further demonstrated in rats made vicious by lesions in the septal area of the brain. The drug dosage which effectively blocked the vicious reaction was well below the dose which caused sedation in these animals.

The LD50 of parenterally administered chlordiazepoxide HCl was determined in mice (72 hours) and rats (5 days), and calculated according to the method of Miller and Tainter, with the following results: mice, IV, 123 ± 12 mg/kg; mice, IM, 366 ± 7 mg/kg; rats, IV, 120 ± 7 mg/kg; rats, IM, > 160 mg/kg.

Effects on Reproduction

Reproduction studies in rats fed 10, 20 and 80 mg/kg daily and bred through one or two matings showed no congenital anomalies, nor were there adverse effects on lactation of the dams or growth of the newborn. However, in another study at 100 mg/kg daily there was noted a significant decrease in the fertilization rate and a marked decrease in the viability and body weight of off-spring which may be attributable to sedative activity, thus resulting in lack of interest in mating and lessened maternal nursing and care of the young. One neonate in each of the first and second matings in the rat reproduction study at the 100 mg/kg dose exhibited major skeletal defects. Further studies are in progress to determine the significance of these findings.

INDICATIONS AND USAGE

Chlordiazepoxide HCl capsules are indicated for the management of anxiety disorders or for the short term relief of symptoms of anxiety, withdrawal symptoms of acute alcoholism, and preoperative apprehension and anxiety. Anxiety or tension associated with the stress of everyday life usually does not require treatment with an anxiolytic.

The effectiveness of chlordiazepoxide HCl capsules in long term use, that is, more than 4 months, has not been assessed by systematic clinical studies. The physician should periodically reassess the usefulness of the drug for the individual patient.

CONTRAINDICATIONS

Chlordiazepoxide HCl capsules are contraindicated in patients with known hypersensitivity to the drug.

WARNINGS

Concomitant use of benzodiazepines, including chlordiazepoxide, and opioids may result in profound sedation, respiratory depression, coma, and death. Because of these risks, reserve concomitant prescribing of these drugs for use in patients for whom alternative treatment options are inadequate.

Observational studies have demonstrated that concomitant use of opioid analgesics and benzodiazepines increases the risk of drug-related mortality compared to use of opioids alone. If a decision is made to prescribe chlordiazepoxide concomitantly with opioids, prescribe the lowest effective dosages and minimum durations of concomitant use, and follow patients closely for signs and symptoms of respiratory depression and sedation. In patients already receiving an opioid analgesic, prescribe a lower initial dose of chlordiazepoxide than indicated in the absence of an opioid and titrate based on clinical response. If an opioid is initiated in a patient already taking chlordiazepoxide, prescribe a lower initial dose of the opioid and titrate based upon clinical response.

Advise both patients and caregivers about the risks of respiratory depression and sedation when chlordiazepoxide is used with opioids. Advise patients not to drive or operate heavy machinery until the effects of concomitant use with the opioid have been determined (see DRUG INTERACTIONS).

Chlordiazepoxide HCl may impair the mental and/or physical abilities required for the performance of potentially hazardous tasks such as driving a vehicle or operating machinery. Similarly, it may impair mental alertness in children. The concomitant use of alcohol or other central nervous system depressants may have an additive effect. PATIENTS SHOULD BE WARNED ACCORDINGLY.

Usage in Pregnancy

An increased risk of congenital malformations associated with the use of minor tranquilizers (chlordiazepoxide, diazepam and meprobamate) during the first trimester of pregnancy has been suggested in several studies. Because use of these drugs is rarely a matter of urgency, their use during this period should almost always be avoided. The possibility that a woman of childbearing potential may be pregnant at the time of institution of therapy should be considered. Patients should be advised that if they become pregnant during therapy or intend to become pregnant they should communicate with their physicians about the desirability of discontinuing the drug.

PRECAUTIONS

In elderly and debilitated patients, it is recommended that the dosage be limited to the smallest effective amount to preclude the development of ataxia or oversedation (10 mg or less per day initially, to be increased gradually as needed and tolerated). In general, the concomitant administration of chlordiazepoxide HCl and other psychotropic agents is not recommended. If such combination therapy seems indicated, careful consideration should be given to the pharmacology of the agents to be employed — particularly when the known potentiating compounds such as MAO inhibitors and phenothiazines are to be used. The usual precautions in treating patients with impaired renal or hepatic function should be observed.

Paradoxical reactions, e.g., excitement, stimulation and acute rage, have been reported in psychiatric patients and in hyperactive aggressive pediatric patients, and should be watched for during chlordiazepoxide HCl therapy. The usual precautions are indicated when chlordiazepoxide HCl is used in the treatment of anxiety states where there is any evidence of impending depression; it should be borne in mind that suicidal tendencies may be present and protective measures may be necessary. Although clinical studies have not established a cause and effect relationship, physicians should be aware that variable effects on blood coagulation have been reported very rarely in patients receiving oral anticoagulants and chlordiazepoxide HCl. In view of isolated reports associating chlordiazepoxide with exacerbation of porphyria, caution should be exercised in prescribing chlordiazepoxide to patients suffering from this disease.

Pediatric Use

Because of the varied response of pediatric patients to CNS-acting drugs, therapy should be initiated with the lowest dose and increased as required (see DOSAGE AND ADMINISTRATION). Since clinical experience with chlordiazepoxide HCl in pediatric patients under 6 years of age is limited, use in this age group is not recommended. Hyperactive aggressive pediatric patients should be monitored for paradoxical reactions to chlordiazepoxide HCl (see PRECAUTIONS).

Information for Patients

To assure the safe and effective use of benzodiazepines, patients should be informed that, since benzodiazepines may produce psychological and physical dependence, it is advisable that they consult with their physician before either increasing the dose or abruptly discontinuing this drug.

DRUG INTERACTIONS

The concomitant use of benzodiazepines and opioids increases the risk of respiratory depression because of actions at different receptor sites in the CNS that control respiration. Benzodiazepines interact at GABAA sites and opioids interact primarily at mu receptors. When benzodiazepines and opioids are combined, the potential for benzodiazepines to significantly worsen opioid-related respiratory depression exists. Limit dosage and duration of concomitant use of benzodiazepines and opioids, and monitor patients closely for respiratory depression and sedation.

ADVERSE REACTIONS

The necessity of discontinuing therapy because of undesirable effects has been rare. Drowsiness, ataxia and confusion have been reported in some patients — particularly the elderly and debilitated. While these effects can be avoided in almost all instances by proper dosage adjustment, they have occasionally been observed at the lower dosage ranges. In a few instances syncope has been reported.

Other adverse reactions reported during therapy include isolated instances of skin eruptions, edema, minor menstrual irregularities, nausea and constipation, extrapyramidal symptoms, as well as increased and decreased libido. Such side effects have been infrequent, and are generally controlled with reduction of dosage. Changes in EEG patterns (low-voltage fast activity) have been observed in patients during and after chlordiazepoxide HCl treatment.

Blood dyscrasias (including agranulocytosis), jaundice and hepatic dysfunction have occasionally been reported during therapy. When chlordiazepoxide HCl treatment is protracted, periodic blood counts and liver function tests are advisable.

DRUG ABUSE AND DEPENDENCE

Chlordiazepoxide hydrochloride capsules are classified by the Drug Enforcement Administration as a Schedule IV controlled substance.

Withdrawal symptoms, similar in character to those noted with barbiturates and alcohol (convulsions, tremor, abdominal and muscle cramps, vomiting and sweating), have occurred following abrupt discontinuance of chlordiazepoxide. The more severe withdrawal symptoms have usually been limited to those patients who had received excessive doses over an extended period of time. Generally milder withdrawal symptoms (e.g., dysphoria and insomnia) have been reported following abrupt discontinuance of benzodiazepines taken continuously at therapeutic levels for several months. Consequently, after extended therapy, abrupt discontinuation should generally be avoided and a gradual dosage tapering schedule followed. Addiction-prone individuals (such as drug addicts or alcoholics) should be under careful surveillance when receiving chlordiazepoxide or other psychotropic agents because of the predisposition of such patients to habituation and dependence.

OVERDOSAGE

Manifestations of chlordiazepoxide overdosage includes somnolence, confusion, coma and diminished reflexes. Respiration, pulse and blood pressure should be monitored, as in all cases of drug overdosage, although, in general, these effects have been minimal following chlordiazepoxide HCl overdosage. General supportive measures should be employed, along with immediate gastric lavage. Intravenous fluids should be administered and an adequate airway maintained. Hypotension may be combated by the use of norepinephrine or metaraminol. Dialysis is of limited value. There have been occasional reports of excitation in patients following chlordiazepoxide HCl overdosage; if this occurs barbiturates should not be used. As with the management of intentional overdosage with any drug, it should be borne in mind that multiple agents may have been ingested.

Flumazenil, a specific benzodiazepine-receptor antagonist, is indicated for the complete or partial reversal of the sedative effects of benzodiazepines and may be used in situations when an overdose with a benzodiazepine is known or suspected. Prior to the administration of flumazenil, necessary measures should be instituted to secure airway, ventilation and intravenous access. Flumazenil is intended as an adjunct to, not as a substitute for, proper management of benzodiazepine overdose. Patients treated with flumazenil should be monitored for resedation, respiratory depression and other residual benzodiazepine effects for an appropriate period after treatment. The prescriber should be aware of a risk of seizure in association with flumazenil treatment, particularly in long term benzodiazepine users and in cyclic antidepressant overdose. The complete flumazenil package insert, including CONTRAINDICATIONS, WARNINGS, and PRECAUTIONS, should be consulted prior to use.

DOSAGE AND ADMINISTRATION

Because of the wide range of clinical indications for chlordiazepoxide HCl, the optimum dosage varies with the diagnosis and response of the individual patient. The dosage, therefore, should be individualized for maximum beneficial effects.

ADULTS | USUAL DAILY DOSE
Relief of Mild and Moderate Anxiety Disorders and Symptoms of Anxiety | 5 mg or 10 mg, 3 or 4 times daily
Relief of Severe Anxiety Disorders and Symptoms of Anxiety | 20 mg or 25 mg, 3 or 4 times daily
Geriatric Patients, or in the presence of; debilitating disease. | 5 mg, 2 to 4 times daily

Preoperative Apprehension and Anxiety

On days preceding surgery, 5 to 10 mg orally, 3 or 4 times daily. If used as preoperative medication, 50 to 100 mg IM 1 hour prior to surgery.

PEDIATRIC PATIENTS | USUAL DAILY DOSE
Because of the varied response of pediatric patients to CNS-acting drugs, therapy should be initiated with the lowest dose and increased as required. Since clinical experience in pediatric patients under 6 years of age is limited, the use of the drug in this age group is not recommended. | 5 mg, 2 to 4 times daily (may be increased in some pediatric patients to 10 mg, 2 to 3 times daily)

For the relief of withdrawal symptoms of acute alcoholism, the parenteral form is usually used initially. If the drug is administered orally, the suggested initial dose is 50 to 100 mg, to be followed by repeated doses as needed until agitation is controlled — up to 300 mg per day. Dosage should then be reduced to maintenance levels. .

HOW SUPPLIED

25 mg are available as a two-piece hard gelatin capsule with an aqua green opaque cap and a white opaque body filled with white powder, imprinted in black ink .

NDC 68071-5256-6 BOTTLES OF 6

stylized barr capsules. Dispense in a tight, light-resistant container as defined in the USP, with a child-resistant closure (as required). Store at 20° to 25°C (68° to 77°F) [See USP Controlled Room Temperature] in a dry place. KEEP THIS AND ALL MEDICATIONS OUT OF THE REACH OF CHILDREN. Teva Pharmaceuticals USA, Inc. North Wales, PA 19454 Rev. D 8/2016

MEDICATION GUIDE

Chlordiazepoxide Hydrochloride (klorʺ dye azʺ e poxʹ ide hyeʺ droe klorʹ ide) Capsules, C-IV

What is the most important information I should know about Chlordiazepoxide HCl?

- Chlordiazepoxide HCl is a benzodiazepine medicine. Taking benzodiazepines with opioid medicines, alcohol, or other central nervous system depressants (CNS) (including street drugs) can cause severe drowsiness, breathing problems (respiratory depression), coma and death. Get emergency help right away if any of the following happens:

- shallow or slowed breathing
- breathing stops (which may lead to the heart stopping)
- excessive sleepiness (sedation)

Do not drive or operate heavy machinery until you know how taking Chlordiazepoxide HCl with opioids affects you.

- Risk of abuse, misuse, and addiction. There is a risk of abuse, misuse, and addiction with benzodiazepines, including Chlordiazepoxide HCl, which can lead to overdose and serious side effects including coma and death.
  - Serious side effects including coma and death have happened in people who have abused or misused benzodiazepines, including Chlordiazepoxide HCl. These serious side effects may also include delirium, paranoia, suicidal thoughts or actions, seizures, and difficulty breathing. Call your healthcare provider or go to the nearest hospital emergency room right away if you get any of these serious side effects.
  - You can develop an addiction even if you take Chlordiazepoxide HCl exactly as prescribed by your healthcare provider.
  - Take Chlordiazepoxide HCl exactly as your healthcare provider prescribed.
  - Do not share your Chlordiazepoxide HCl with other people.
  - Keep Chlordiazepoxide HCl in a safe place and away from children.
- Physical dependence and withdrawal reactions. Chlordiazepoxide HCl can cause physical dependence and withdrawal reactions, especially if you continue to take Chlordiazepoxide HCl for several days to several weeks.

- Do not suddenly stop taking Chlordiazepoxide HCl. Stopping Chlordiazepoxide HCl suddenly can cause serious and life-threatening side effects, including unusual movements, responses, or expressions, seizures, sudden and severe mental or nervous system changes, depression, seeing or hearing things that others do not see or hear, an extreme increase in activity or talking, losing touch with reality, and suicidal thoughts or actions. Call your healthcare provider or go to the nearest hospital emergency room right away if you get any of these symptoms.
- Some people who suddenly stop benzodiazepines have symptoms that can last for several weeks to more than 12 months , including, anxiety, trouble remembering, learning, or concentrating, depression, problems sleeping feeling like insects are crawling under your skin, weakness, shaking, muscle twitching, burning or prickling feeling in your hands, arms, legs or feet, and ringing in your ears.
- Physical dependence is not the same as drug addiction. Your healthcare provider can tell you more about the differences between physical dependence and drug addiction.
- Do not take more Chlordiazepoxide HCl than prescribed or take Chlordiazepoxide HCl for longer than prescribed.

What is Chlordiazepoxide HCl?

- Chlordiazepoxide HCl is a prescription medicine used:
  - to treat anxiety disorders
  - for the short-term relief of the symptoms of anxiety
  - to treat withdrawal symptoms of acute alcoholism
  - preoperatively to treat apprehension and anxiety
- Chlordiazepoxide HCl is a federal controlled substance (C-IV) because it contains chlordiazepoxide that can be abused or lead to dependence. Keep Chlordiazepoxide HCl in a safe place to prevent misuse and abuse. Selling or giving away Chlordiazepoxide HCl may harm others, and is against the law. Tell your healthcare provider if you have abused or been dependent on alcohol, prescription medicines or street drugs.
- It is not known if Chlordiazepoxide HCl is safe and effective in children under 6 years of age.
- It is not known if Chlordiazepoxide HCl is safe and effective for use for longer than 4 months.

Do not take Chlordiazepoxide HCl if you are allergic to chlordiazepoxide or to any of the ingredients in Chlordiazepoxide HCl capsules. See the end of this Medication Guide for a complete list of ingredients in Chlordiazepoxide HCl capsules.

Before you take Chlordiazepoxide HCl, tell your healthcare provider about all of your medical conditions, including if you:

- have or have had depression, mood problems, or suicidal thoughts or behavior
- have a history of drug or alcohol abuse or addiction
- have liver or kidney problems
- are pregnant or plan to become pregnant. Chlordiazepoxide HCl may harm your unborn baby. You and your healthcare provider should decide if you should take Chlordiazepoxide HCl while you are pregnant.
- are breastfeeding or plan to breastfeed. Chlordiazepoxide HCl may pass into your breast milk and may harm your baby. Talk to your healthcare provider about the best way to feed your baby if you take Chlordiazepoxide HCl.

Tell your healthcare provider about all the medicines you take, including prescription and over-the-counter medicines, vitamins, and herbal supplements.

Taking Chlordiazepoxide HCl with certain other medicines can cause side effects or affect how well Chlordiazepoxide HCl or the other medicines work.

Ask your healthcare provider if you are not sure if you are taking any of these medicines. Your healthcare provider can tell you if it is safe to take Chlordiazepoxide HCl with your other medicines.

Do not start or stop any other medicines during treatment with Chlordiazepoxide HCl without talking to your healthcare provider first. Stopping Chlordiazepoxide HCl suddenly may cause you to have serious side effects. See, “What are the possible side effects of Chlordiazepoxide HCl?”

Know the medicines you take. Keep a list of them to show to your healthcare provider and pharmacist when you get a new medicine.

How should I take Chlordiazepoxide HCl?

- Take Chlordiazepoxide HCl exactly as your healthcare provider tells you to take it.
- If you take too much Chlordiazepoxide HCl, call your healthcare provider or go to the nearest hospital emergency room right away.

What are the possible side effects of Chlordiazepoxide HCl?

Chlordiazepoxide HCl may cause serious side effects, including:

- See “What is the most important information I should know about Chlordiazepoxide HCl?”
- Chlordiazepoxide HCl can make you sleepy or dizzy and can slow your thinking and motor skills.

- Do not drive, operate heavy machinery, or do other dangerous activities until you know how Chlordiazepoxide HCl affects you.
- Do not drink alcohol or take other drugs that may make you sleepy or dizzy while taking Chlordiazepoxide HCl without first talking to your healthcare provider. When taken with alcohol or drugs that cause sleepiness or dizziness, Chlordiazepoxide HCl may make your sleepiness or dizziness much worse.

The most common side effects of Chlordiazepoxide HCl include:

- drowsiness

- loss of control of body movements (ataxia)

- confusion

These are not all the possible side effects of chlordiazepoxide. Call your doctor for medical advice about side effects. You may report side effects to FDA at 1-800-FDA-1088.

How should I store Chlordiazepoxide HCl?

- Store Chlordiazepoxide HCl at room temperature between 68°F to 77°F (20°C to 25°C).
- Keep Chlordiazepoxide HCl capsules in a tightly closed container and out of the light.
- Keep Chlordiazepoxide HCl and all medicines out of the reach of children.

General information about the safe and effective use of Chlordiazepoxide HCl.

Medicines are sometimes prescribed for purposes other than those listed in a Medication Guide. Do not use Chlordiazepoxide HCl for a condition for which it was not prescribed. Do not give Chlordiazepoxide HCl to other people, even if they have the same symptoms that you have. It may harm them. You can ask your pharmacist or healthcare provider for information about Chlordiazepoxide HCl that is written for health professionals.

What are the ingredients in Chlordiazepoxide HCl?

Active ingredient: chlordiazepoxide hydrochloride

Inactive ingredients: anhydrous lactose, D&C yellow no. 10, FD&C blue no. 1, FD&C blue no. 1 aluminum lake, gelatin, hydrogenated vegetable oil, microcrystalline cellulose, pharmaceutical glaze, and titanium dioxide. The 5 mg and 25 mg also contain D&C yellow no. 10 aluminum lake, FD&C blue no. 2 aluminum lake, FD&C red no. 40 aluminum lake, propylene glycol, and synthetic black iron oxide. In addition, the 5 mg contains D&C red no. 33 and the 10 mg also contains butyl paraben, edetate calcium disodium, dimethyl polysiloxane, ethylene glycol monoethyl ether, FD&C red no. 40, methyl paraben, propyl paraben, sodium, sodium lauryl sulfate, sodium propionate, and soya lecithin.

Manufactured For:

Teva Pharmaceuticals USA, Inc.

North Wales, PA 19454

For more information, go to www.tevagenerics.com or call 1-888-838-2872.

This Medication Guide has been approved by the U.S. Food and Drug Administration Rev. D 1/2021